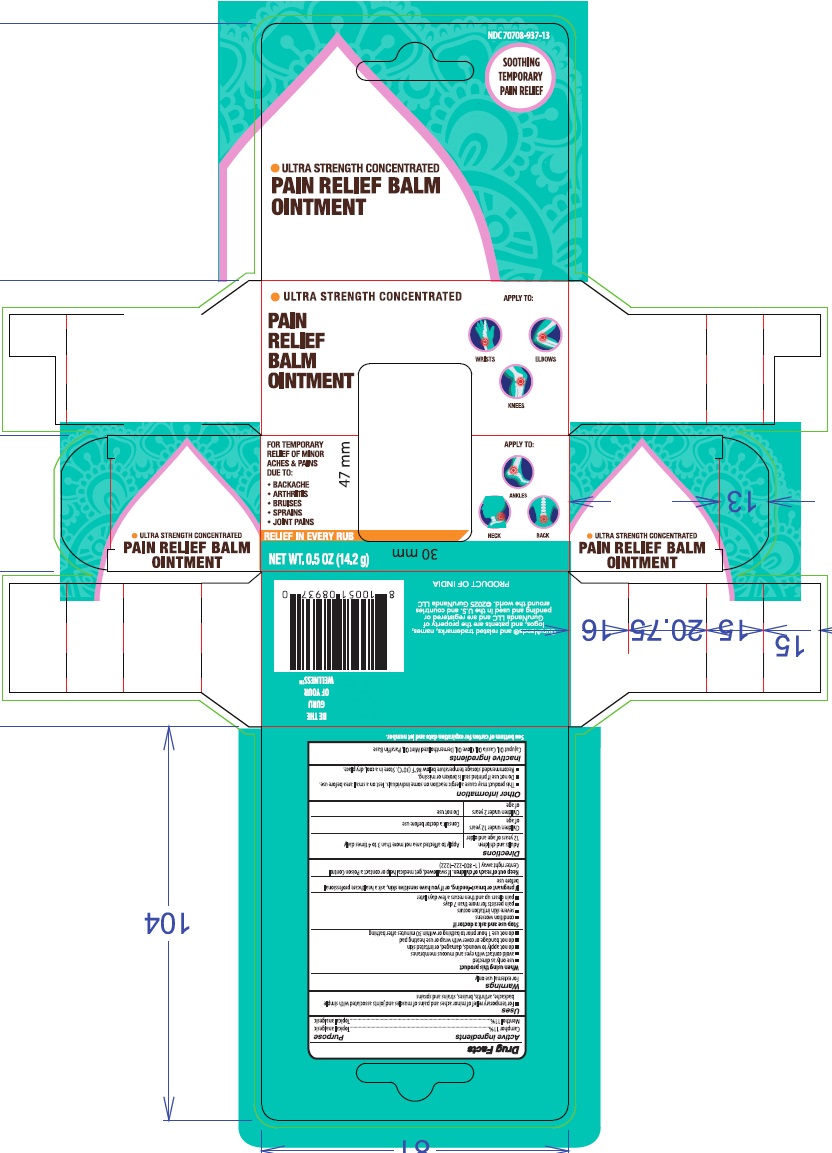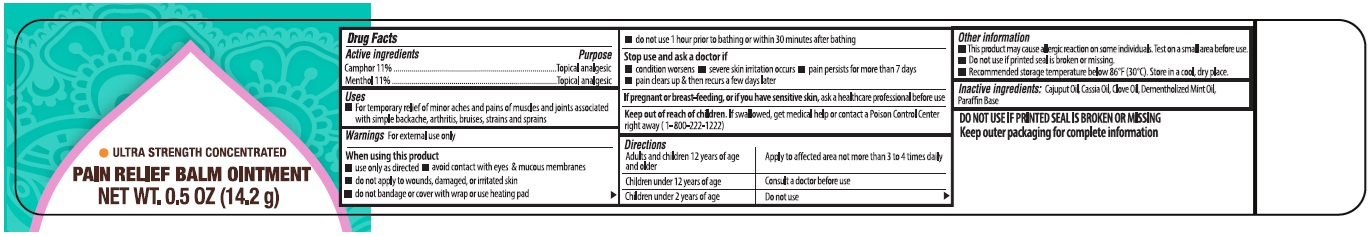 DRUG LABEL: Pain Relief Balm
NDC: 73492-718 | Form: OINTMENT
Manufacturer: ALAINA HEALTHCARE PRIVATE LIMITED
Category: otc | Type: HUMAN OTC DRUG LABEL
Date: 20251209

ACTIVE INGREDIENTS: MENTHOL 110 mg/1 g; CAMPHOR (SYNTHETIC) 110 mg/1 g
INACTIVE INGREDIENTS: CAJUPUT OIL; CHINESE CINNAMON OIL; CLOVE OIL; PEPPERMINT OIL; PARAFFIN

Pain Relief Balm Ointment
Drug Facts

Active Ingredients Purpose

Camphor 11%...................................................Topical analgesic

Menthol 11%....................................................Topical analgesic

Uses

- For temporary relief of minor aches and pains of muscles and joints associated with simple backache, arthritis, bruises, strains and sprains

Warnings

For external use only

When using this product

- use only as directed
- avoid contact with eyes & mucous membranes
- do not apply to wounds, damaged, or irritated skin
- do not bandage or cover with wrap or use heating pad
- do not use 1 hour prior to bathing or within 30 minutes after bathing

Stop use and ask a doctor if

- condition worsens
- severe skin irritation occurs
- pain persists for more than 7 days
- pain clears up & then recurs a few days later

PREGNANCY OR BREAST FEEDING

If pregnant or breast-feeding, or if you have sensitive skin, ask a healthcare professional before use

Keep out of reach of children.If swallowed, get medical help or contact a Poison Control Center right away (1-800-222-1222).

Directions

Adults and children 12 years of age and older | Apply to affected area not more than 3 to 4 times daily
Children under 12 years of age | Consult a doctor before use
Children under 2 years of age | Do not use

Other information

- This product may cause allergic reaction on some individuals. Test on a small area before use.
- Do not use if printed seal is broken or missing
- Recommended storage temperature below 86°F (30°C). Store in a cool, dry place.

Inactive ingredients

Cajuput Oil, Cassia Oil, Clove Oil, Dementholized Mint Oil, Paraffin Base

Questions?

Call XXX-XXX-XXXX

PRINCIPAL DISPLAY PANEL

Pain Relief Balm Ointment 0.5 oz (14.2g) - NDC 73492-718-15 - Container Label

Pain Relief Balm Ointment 0.5 oz (14.2g) - NDC 73492-718-15 - Carton Label